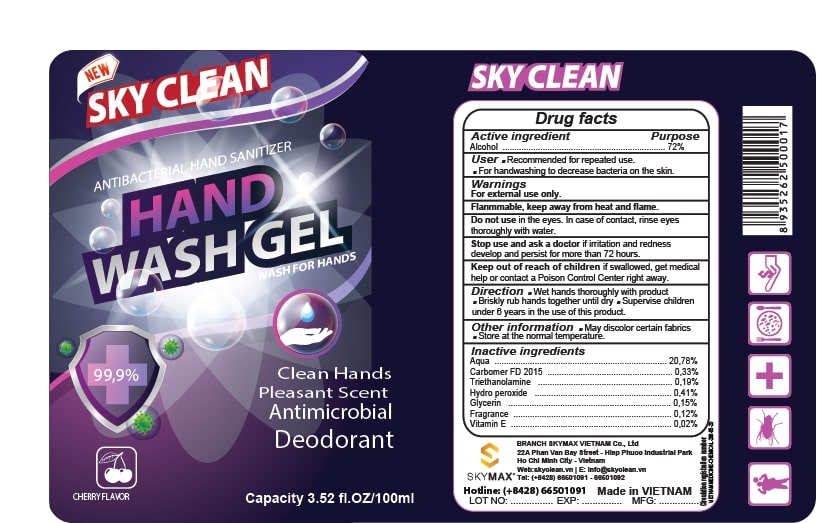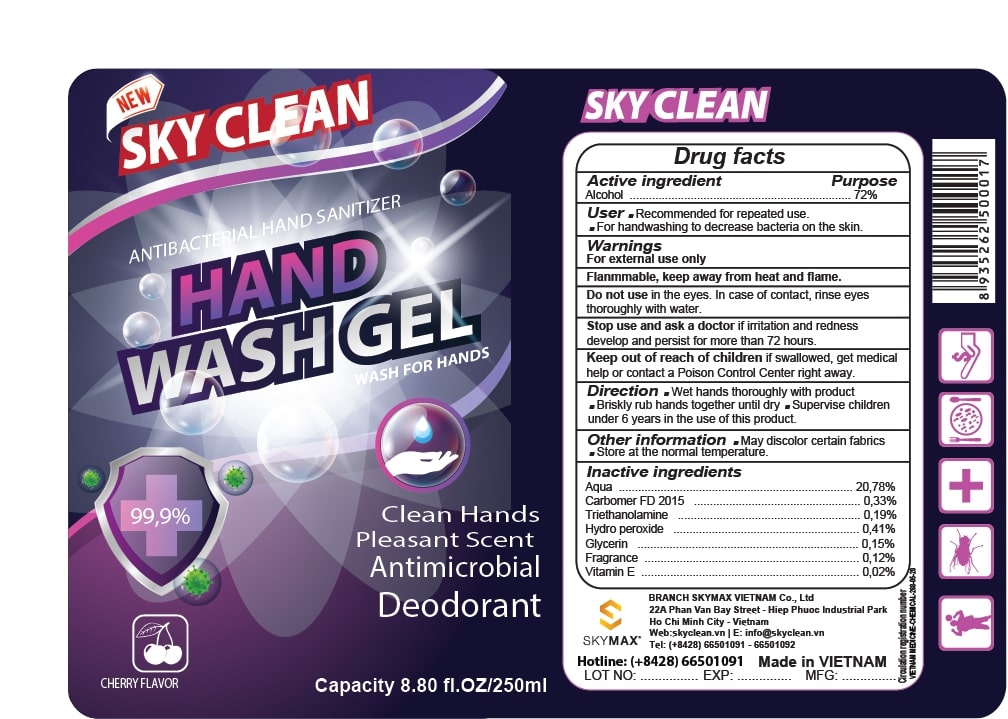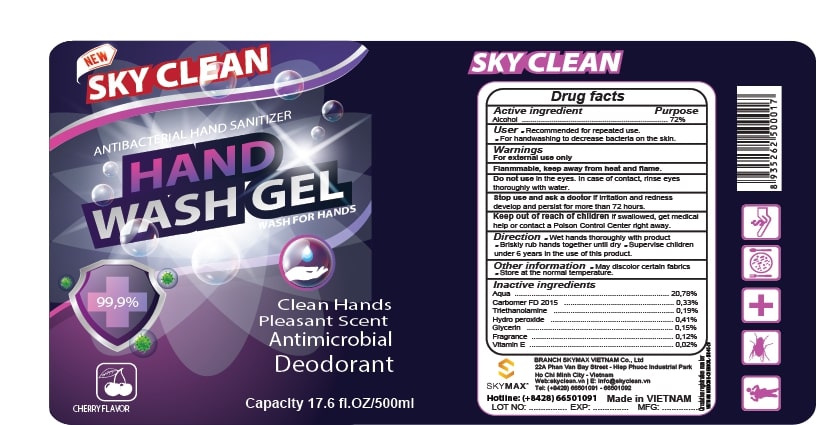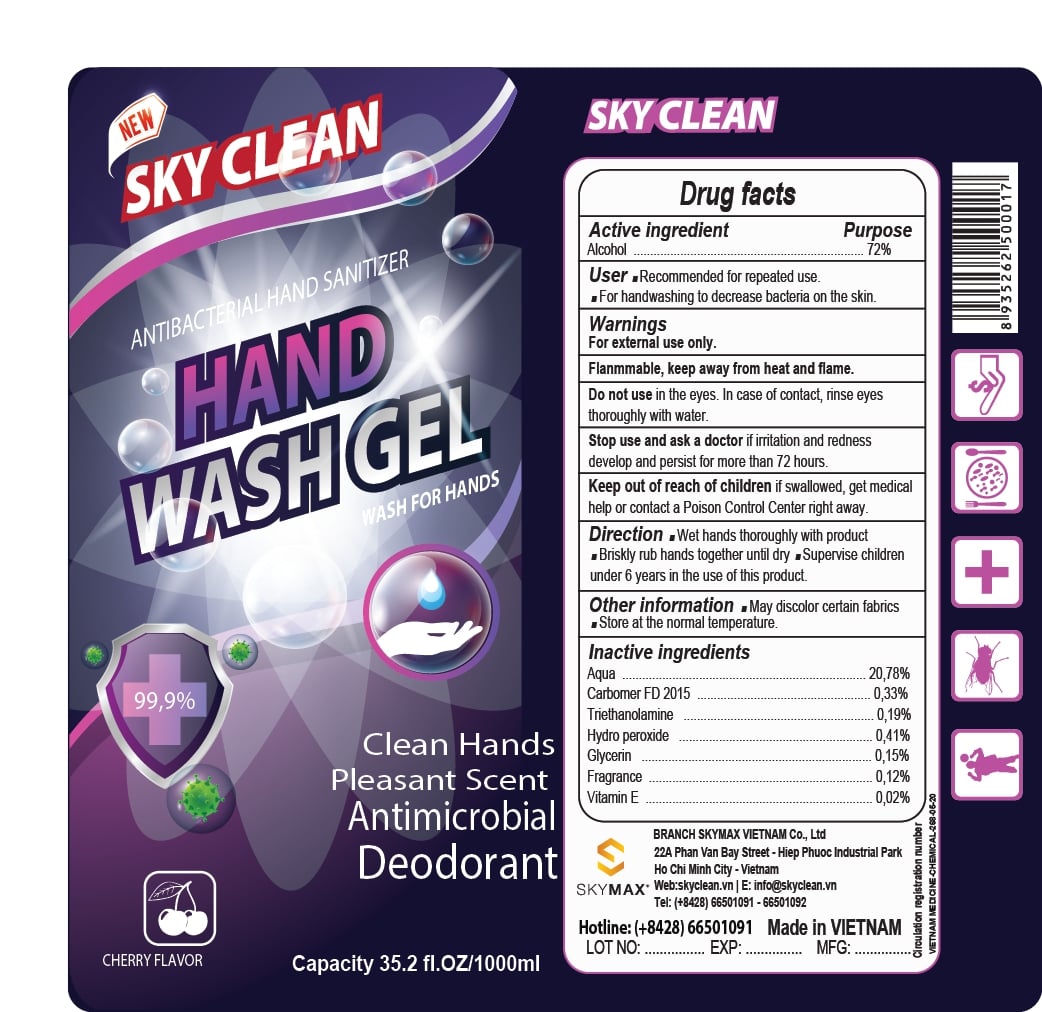 DRUG LABEL: Hand Sanitizer
NDC: 81650-100 | Form: GEL
Manufacturer: SKYMAX VIETNAM COMPANY LIMITED
Category: otc | Type: HUMAN OTC DRUG LABEL
Date: 20210310

ACTIVE INGREDIENTS: ALCOHOL 72 mL/100 mL
INACTIVE INGREDIENTS: .ALPHA.-TOCOPHEROL 0.02 mL/100 mL; TROLAMINE 0.19 mL/100 mL; CARBOMER 940 0.33 mL/100 mL; GLYCERIN 0.15 mL/100 mL; HYDROGEN PEROXIDE 0.41 mL/100 mL; WATER 20.78 mL/100 mL

Active Ingredient(s)

Alcohol 80% v/v. Purpose: Antiseptic

Purpose

Antiseptic, Hand Sanitizer

Use

Recommended for repeated use.

For handwashing to decrease bacteria on the skin.

Warnings

For external use only. Flammable. Keep away from heat or flame

Do not use

- in the eyes. In case of contact, rinse eyes thoroughly with water

Stop use and ask a doctor if irritation and redness develop and persist for more than 72 hours.
Keep out of reach of children. If swallowed, get medical help or contact a Poison Control Center right away.

Stop use and ask a doctor if irritation or rash occurs. These may be signs of a serious condition.

Keep out of reach of children. If swallowed, get medical help or contact a Poison Control Center right away.

Directions

- We hands thoroughly with product
- Brisky rub hands together until dry
- Supervise children under 6 years in the use of this product.

Other information

- May discolor certain fabrics
- Store at the normal temperature

Inactive ingredients

aqua, carbomer 940, trolamine, hydro peroxide, glycerin, fragrance, vitamin e

RECENT MAJOR CHANGES

Indications and Usage: Change wordings

Directions: Change wordings

Package Label - Principal Display Panel

100 mL NDC: 81650-100- 01

250 mL NDC: 81650-100- 02

500 mL NDC: 81650-100- 03

1000 mL NDC: 81650-100- 04